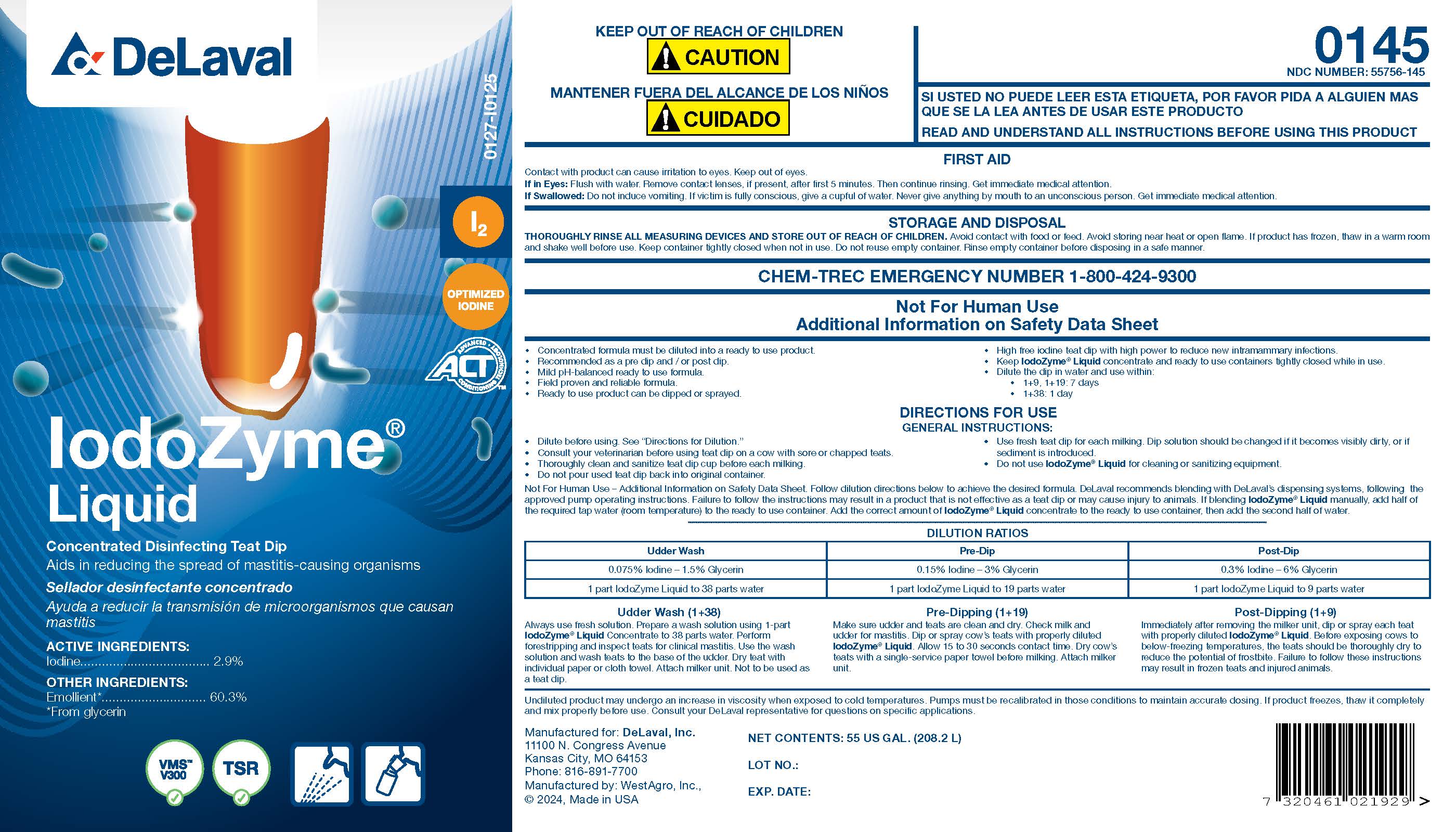 DRUG LABEL: Iodozyme Liquid
NDC: 55756-145 | Form: SOLUTION, CONCENTRATE
Manufacturer: DeLaval, Inc.
Category: animal | Type: OTC ANIMAL DRUG LABEL
Date: 20250306

ACTIVE INGREDIENTS: IODINE 0.029 g/1 L
INACTIVE INGREDIENTS: GLYCERIN; DOCUSATE SODIUM; DECYL GLUCOSIDE; SODIUM IODIDE; PHOSPHORIC ACID; SODIUM HYDROXIDE; WATER; FD&C YELLOW NO. 5

DeLaval IodoZyme® Liquid

PURPOSE

Concentrated Disinfecting Teat Dip

Aids in reducing the spread of mastitis-causing organisms

ACTIVE INGREDIENTS:
Iodine ................................................................... 2.9%

OTHER INGREDIENTS:

Emollient* ..................... 60.3%

*From glycerin

INDICATIONS AND USAGE

- Concentrated formula must be diluted into a ready to use product.
- Recommended as a per dip and / or post dip.
- Mild pH-balanced ready to use formula.
- Field proven and reliable formula.
- Ready to use product can be dipped or sprayed.
- Hight free iodine teat dip with high power to reduce new intramammary infections.
- Keep IodoZyme® Liquid concentrate and ready to use containers tightly closed while in use.
- Dilute the dip in water and use within:
- 1+9, 1+19: 7 days
- 1+38: 1 day

DIRECTIONS FOR USE

GENERAL INSTRUCTIONS:

- Dilute before using. See "Directions for Dilution."
- Consult your veterinarian before using teat dip on a cow with sore or chapped teats.
- Thoroughly clean and sanitize teat dip cup before each milking.
- Do not pour used teat dip back into original container.
- Use fresh teat dip for each milking. Dip solution should be changed if it becomes visibly dirty, or if sediment is introduced.
- Do not use IodoZyme® Liquid for cleaning or sanitizing equipment.

Not For Human Use - Additional information on Safety Data Sheet. Follow dilution directions below to achieve the desired formula. DeLaval recommends blending with DeLaval's dispensing systems, following the approved pump operating instructions. Failure to follow the instructions may result in a product that is not as effective as a teat dip or may cause injury to animals. If blending IodoZyme® Liquid manually, add half of the required tap water (room temperature) to the ready to use container. Add the correct amount of IodoZyme® Liquid concentrate to the ready to use container, then add the second half of water.

DILUTION RATIOS
Udder Wash | Pre-Dip | Post-Dip
0.075% Iodine - 1.5% Glycerin | 0.15% Iodine - 3% Glycerin | 0.3% Iodine - 6% Glycerin
1 part IodoZyme Liquid to 38 parts water | 1 part IodoZyme Liquid to 19 parts water | 1 part IodoZyme Liquid to 9 parts water

Udder Wash (1+38)

Always us fresh solution. Prepare a wash solution using 1-part IodoZyme® Liquid Concentrate to 38 parts water. Perform forestripping and inspect teats for clinical mastitis. Use the wash solution and wash teats to the base of the udder. Dry teat with individual paper or cloth towel. Attach milker unit. Not to be used as a teat dip.

Pre-Dipping (1+19)

Made sure udder and teats are clean and dry. Check milk and udder for mastitis. Dip or spray cow's teats with properly diluted IodoZyme® Liquid. Allow 15 to 30 seconds contact time. Dry cow's teats with a single-service paper towel before milking. Attach milker unit.

Post-Dipping (1+9)

Immediately after removing the milker unit, dip or spray each teat with properly diluted IodoZyme® Liquid. Before exposing cows to below-freezing temperatures, the teats should be thoroughly dry to reduce the potential of frostbite. Failure to follow these instructions may result in frozen teats and injured animals.

CHEMTREC EMERGENCY #

1-800-424-9300

KEEP OUT OF REACH OF CHILDREN

! CAUTION

MANTENER FUERA DEL ALCANCE DE LOS NINOS

! CUIDADO

FIRST AIDContact with product can cause irritation to eyes. Keep out of eyes.
If in Eyes: Flush with water. Remove contact lenses, if present, after first 5 minutes. Then continue rinsing. Get immediate medical attention.
If Swallowed: Do not induce vomiting. If victim is fully conscious, give a cupful of water. Never give anything by mouth to an unconscious person. Get immediate medical attention.

WARNINGS AND PRECAUTIONS

READ AND UNDERSTAND ALL INSTRUCTIONS BEFORE USING THIS PRODUCT

Not For Human Use

Additional Information on Safety Data Sheet

STORAGE AND DISPOSAL:

THOROUGHLY RINSE ALL MEASURING DEVICES AND STORE OUT OF REACH OF CHILDREN. Avoid contact with food or feed. Avoid storing near heat or open flame. If product has frozen, thaw in a warm room and shake well before use. Keep container tightly closed when not in use. Do not reuse empty container. Rinse empty container before disposing in a safe manner.

NET CONTENTS: US GAL (L)

LOT NO.:

EXP. DATE:

PACKAGE LABEL

Add image transcription here...